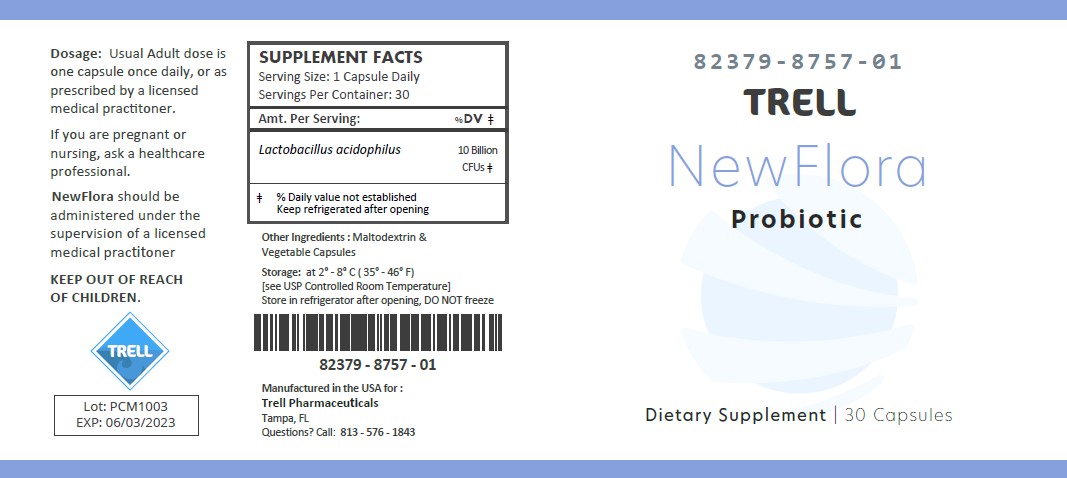 DRUG LABEL: NewFlora
NDC: 82379-8757 | Form: CAPSULE
Manufacturer: Trell Pharma
Category: other | Type: DIETARY SUPPLEMENT
Date: 20220308

ACTIVE INGREDIENTS: LACTOBACILLUS ACIDOPHILUS 10000000000 [CFU]/1 1
INACTIVE INGREDIENTS: MALTODEXTRIN

NewFlora

STATEMENT OF IDENTITY

NewFlora

Other Ingredients: Maltodextrin, Vegetable Capsule.

NewFlora is an orally administered prescription probiotic formulation for the clinical dietary management of suboptimal nutritional status in patients where advanced supplementation is required and nutritional supplementation in physiologically stressful conditions for maintenance of good health is needed.

NewFlora should be administered under the supervision of a licensed medical practitioner.

NewFlora is manufactured in accordance with Current Good Manufacturing Practice for foods, using ingredients that have been approved by the U.S. Food and Drug Administration (FDA) as food additives or are Generally Recognized as Safe (GRAS) for their intended use.

DOSAGE

Usual Adult dose is one capsule once daily, or as prescribed by a licensed medical practitioner.
If you are pregnant or nursing, ask a healthcare professional.

NewFlora should be administered under the supervision of a licensed medical practitioner.

SAFE HANDLING

This product is contraindicated in patients with a known hypersensitivity to any of the ingredients.

NewFlora should only be used under the direction and supervision of a licensed medical practitioner. Use with caution in patients that may have a medical condition, are pregnant, lactating, trying to conceive, under the age of 18, or taking medications.

KEEP OUT OF REACH OF CHILDREN

STORAGE

Store at 2° to 8°C (35° to 46°F).
Store in the refrigerator after opening, DO NOT freeze.

HOW SUPPLIED HEALTH CLAIM

NewFlora, Probiotic

Dietary Supplement

NHRIC: 82379-8757-01 *

Bottles contain 30 Capsules

Distributed by:
Trell Pharma
Tampa, FL

*Does not represent these product codes to be National Drug Codes (NDC). Product codes are formatted according to standard industry practice, to meet the formatting requirement by pedigree reporting and supply-chain control including pharmacies.

† The most appropriate way to ensure pedigree reporting consistent with these regulatory guidelines and safety monitoring is to dispense this product by prescription. This is not an Orange Book product. This product may be administered only under a physician’s supervision and all prescriptions using this product shall be pursuant to state statutes as applicable. The ingredients, indication or claims of this product are not to be construed to be drug claims.